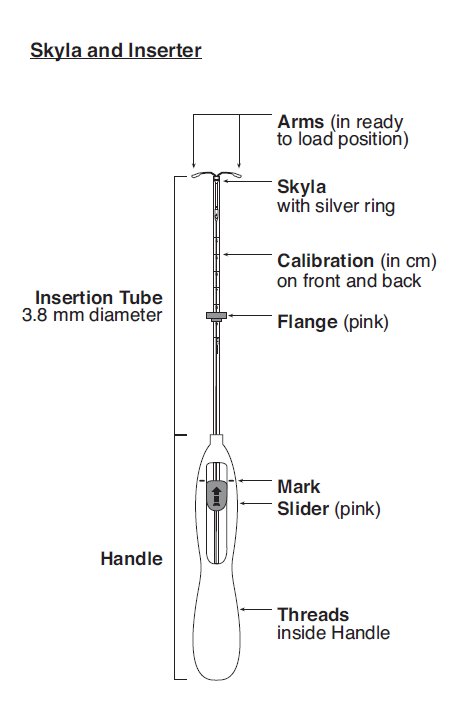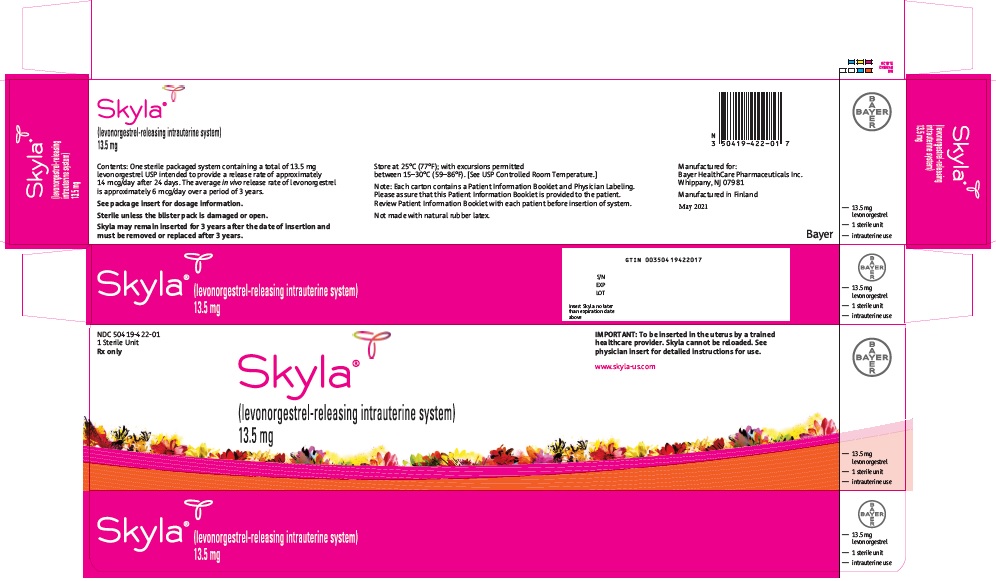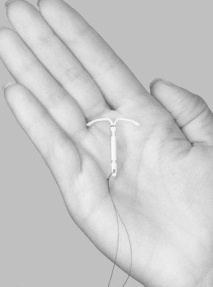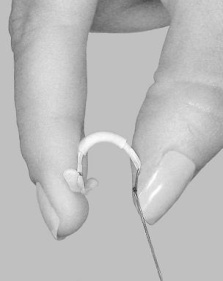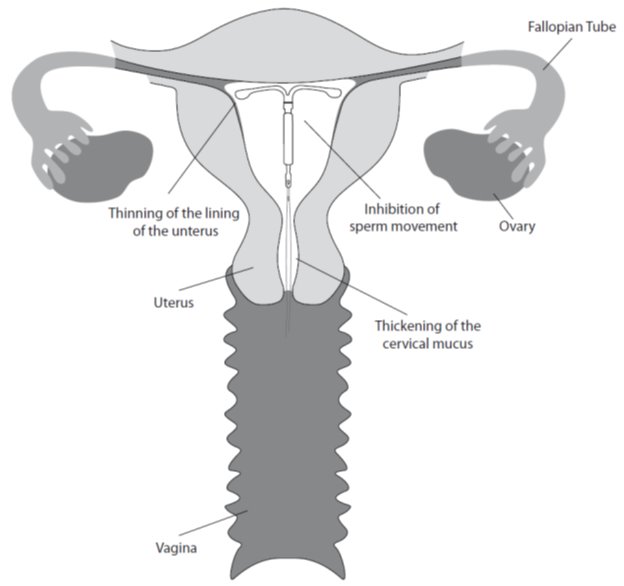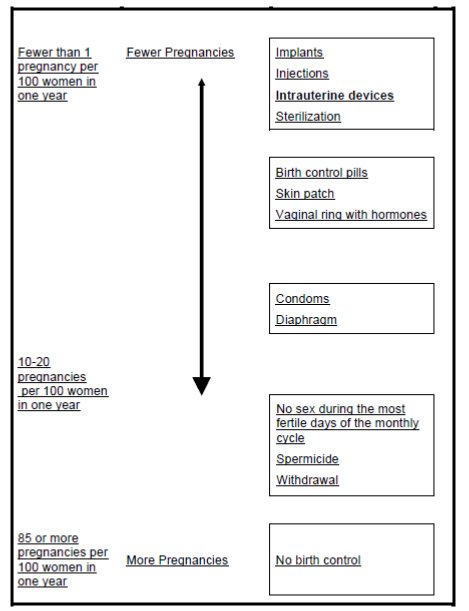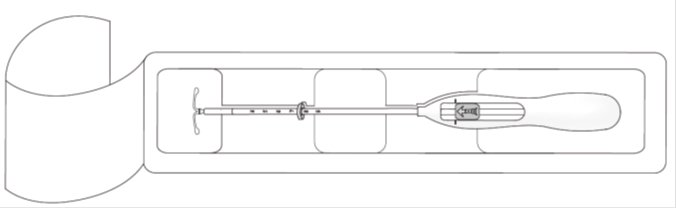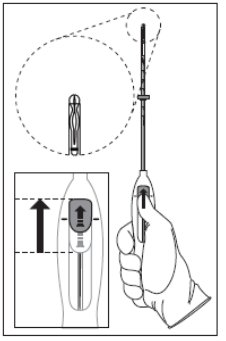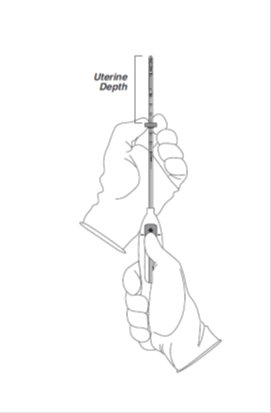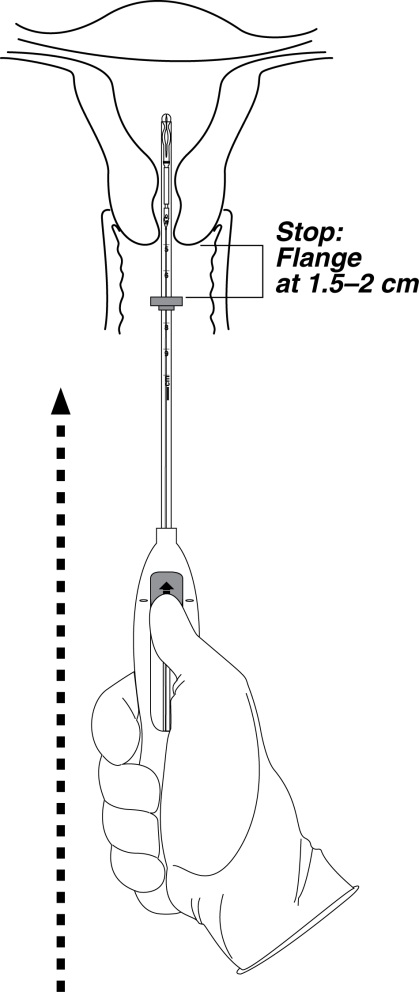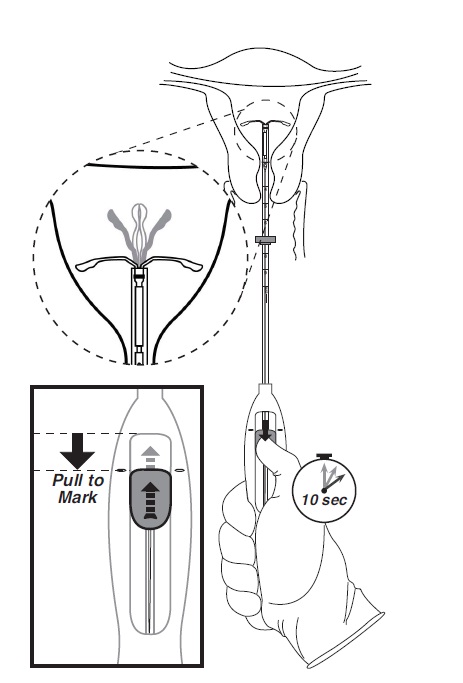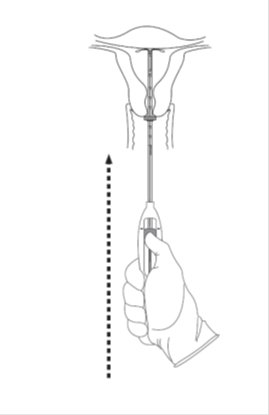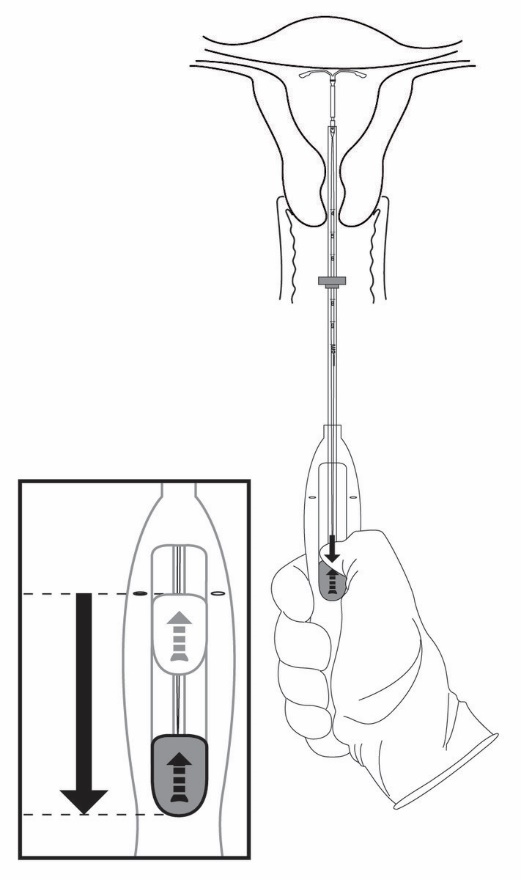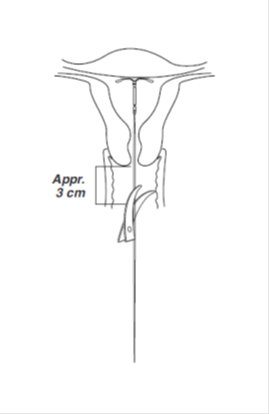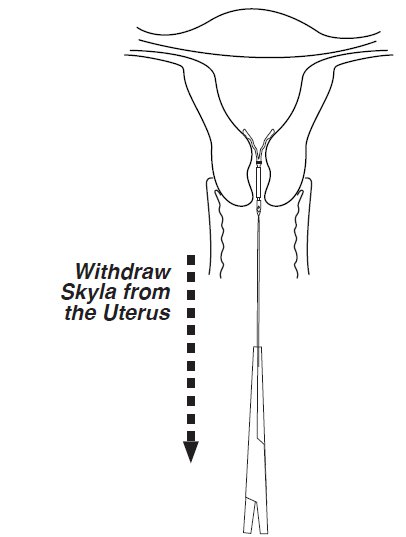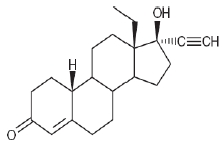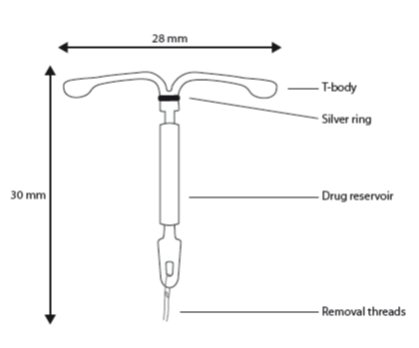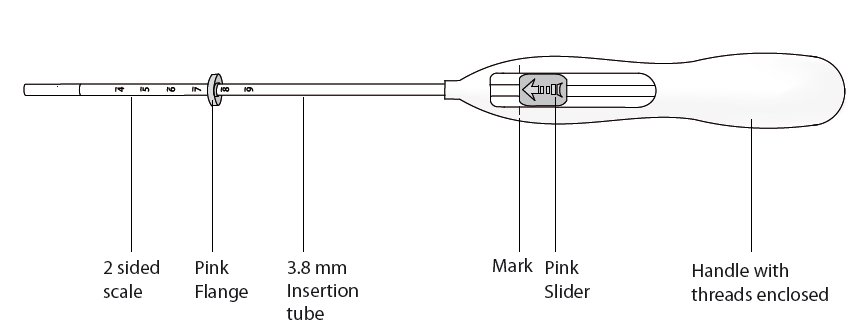 DRUG LABEL: Skyla
NDC: 50419-422 | Form: INTRAUTERINE DEVICE
Manufacturer: Bayer HealthCare Pharmaceuticals Inc.
Category: prescription | Type: HUMAN PRESCRIPTION DRUG LABEL
Date: 20251216

ACTIVE INGREDIENTS: LEVONORGESTREL 13.5 mg/1 1
INACTIVE INGREDIENTS: DIMETHICONE, UNSPECIFIED; BARIUM SULFATE

HIGHLIGHTS OF PRESCRIBING INFORMATION

These highlights do not include all the information needed to use SKYLA safely and effectively. See full prescribing information for SKYLA.
SKYLA (levonorgestrel-releasing intrauterine system)
Initial U.S. Approval: 2000

RECENT MAJOR CHANGES

Dosage and Administration (2.4) 3/2023

1 INDICATIONS AND USAGE

Skyla is a progestin-containing intrauterine system (IUS) indicated for prevention of pregnancy for up to 3 years. (1)

2 DOSAGE AND ADMINISTRATION

- Release rate of levonorgestrel (LNG) is 14 mcg/day after 24 days and declines to 5 mcg/day after 3 years; Skyla must be removed or replaced after 3 years. (2.1)
- To be inserted by a trained healthcare provider using strict aseptic technique. Follow insertion instructions exactly as described. (2.2)
- Patient should be re-examined and evaluated 4 to 6 weeks after insertion; then, yearly or more often if clinically indicated. (2.3)

3 DOSAGE FORMS AND STRENGTHS

- One sterile intrauterine system consisting of a T-shaped polyethylene frame with a steroid reservoir containing 13.5 mg levonorgestrel packaged within a sterile inserter (3)

4 CONTRAINDICATIONS

- Pregnancy or suspicion of pregnancy. Cannot be used for post-coital contraception (emergency contraception) (4)
- Congenital or acquired uterine anomaly if it distorts the uterine cavity (4)
- Acute pelvic inflammatory disease (PID) or a history of PID unless there has been a subsequent intrauterine pregnancy (4)
- Postpartum endometritis or infected abortion in the past 3 months (4)
- Known or suspected uterine or cervical malignancy (4)
- Known or suspected breast cancer or other progestin-sensitive cancer (4)
- Uterine bleeding of unknown etiology (4)
- Untreated acute cervicitis or vaginitis or other lower genital tract infections (4)
- Acute liver disease or liver tumor (benign or malignant) (4)
- Increased susceptibility to pelvic infection (4)
- A previous intrauterine device (IUD) that has not been removed (4)
- Hypersensitivity to any component of Skyla (4)

5 WARNINGS AND PRECAUTIONS

- Remove Skyla if pregnancy occurs with Skyla in place. If a pregnancy occurs, there is increased risk of ectopic pregnancy including loss of fertility, pregnancy loss, septic abortion (including septicemia, shock and death), and premature labor and delivery. (5.1, 5.2)
- Group A streptococcal infection has been reported following insertion of LNG IUS; strict aseptic technique is essential during insertion. (5.3)
- Before using Skyla, consider the risks of PID. (5.4)
- Uterine perforation may occur and may reduce contraceptive effectiveness or require surgery. Risk is increased if inserted in lactating women and may be increased if inserted in women with fixed retroverted uteri and postpartum. (5.5)
- Partial or complete expulsion may occur, which can be unnoticed, leading to loss of contraceptive efficacy. (5.6)
- Evaluate persistent enlarged ovarian follicles or ovarian cysts. (5.7)
- Bleeding patterns become altered, may remain irregular and amenorrhea may ensue. (5.8)
- Skyla can be safely scanned with MRI only under certain conditions (5.11)

6 ADVERSE REACTIONS

The most common adverse reactions reported (>10% users) are bleeding pattern alterations, vulvovaginitis, abdominal/pelvic pain, acne/seborrhea, headache/migraine, ovarian cyst and dysmenorrhea/uterine spasm. (6)

To report SUSPECTED ADVERSE REACTIONS, contact Bayer HealthCare Pharmaceuticals Inc. at 1-888-842-2937 or FDA at 1-800-FDA-1088 or www.fda.gov/medwatch.

FULL PRESCRIBING INFORMATION

1 INDICATIONS AND USAGE

Skyla® is indicated to prevent pregnancy for up to 3 years.

Replace the system after 3 years if continued use is desired.

2 DOSAGE AND ADMINISTRATION

2.1 Dosing Over Time

Skyla contains 13.5 mg of levonorgestrel (LNG) released in vivo at a rate of approximately 14 mcg/day after 24 days. This rate decreases progressively to approximately 6 mcg/day after 1 year and to 5 mcg/day after 3 years. The average in vivo release rate of LNG is approximately 8 mcg/day over the first year of use and 6 mcg/day over a period of 3 years. [See Clinical Pharmacology (12.3).]

Skyla must be removed by the end of the third year and can be replaced at the time of removal with a new Skyla if continued contraceptive protection is desired.

Skyla can be physically distinguished from other intrauterine systems (IUSs) by the combination of the visibility of the silver ring on ultrasound and the brown color of the removal threads.

Skyla is supplied in a sterile package within an inserter that enables single-handed loading (see Figure 1). Do not open the package until required for insertion [see Description (11.2)]. Do not use if the seal of the sterile package is broken or appears compromised. Use strict aseptic techniques throughout the insertion procedure [see Warnings and Precautions (5.3)].

2.2. Insertion Instructions

- Obtain a complete medical and social history to determine conditions that might influence the selection of a levonorgestrel-releasing intrauterine system (LNG IUS) for contraception. If indicated, perform a physical examination, and appropriate tests for any forms of genital or other sexually transmitted infections. [See Contraindications (4) and Warnings and Precautions (5.10).] Because irregular bleeding/spotting is common during the first months of Skyla use, exclude endometrial pathology (polyps or cancer) prior to the insertion of Skyla in women with persistent or uncharacteristic bleeding [see Warnings and Precautions (5.8)].
- Follow the insertion instructions exactly as described to ensure proper placement and avoid premature release of Skyla from the inserter. Once released, Skyla cannot be re-loaded.
- Skyla should be inserted by a trained healthcare provider. Healthcare providers should become thoroughly familiar with the insertion instructions before attempting insertion of Skyla.
- Insertion may be associated with some pain and/or bleeding or vasovagal reactions (for example, syncope, bradycardia) or with seizure, especially in patients with a predisposition to these conditions. Consider administering analgesics prior to insertion.

Timing of Insertion

Table 1: When to Insert Skyla
Starting Skyla in women not currently using hormonal or intrauterine contraception | - Insert Skyla any time there is reasonable certainty that the woman is not pregnant. Consider the possibility of ovulation and conception prior to initiation of this product [see Contraindications (4)]. - If Skyla is inserted during the first seven days of the menstrual cycle or immediately after a first trimester abortion, back-up contraception is not needed. - If Skyla is not inserted during the first seven days of the menstrual cycle, a barrier method of contraception should be used, or the patient should abstain from vaginal intercourse for seven days to prevent pregnancy.
Switching to Skyla from an oral, transdermal or vaginal hormonal contraceptive | - Insert Skyla at any time, including during the hormone-free interval of the previous method. - If inserted during active use of the previous method, continue that method for 7 days after Skyla insertion or until the end of the current treatment cycle. - If the woman was using continuous hormonal contraception, discontinue that method seven days after Skyla insertion.
Switching to Skyla from an injectable progestin contraceptive | - Insert Skyla at any time; a non-hormonal back-up birth control (such as condoms or spermicide) should also be used for 7 days if Skyla is inserted more than 3 months (13 weeks) after the last injection.
Switching to Skyla from a contraceptive implant or another IUS | - Insert Skyla on the same day the implant or IUS is removed. - Insert Skyla at any time during the menstrual cycle.
Inserting Skyla after first trimester abortion or miscarriage | - Insert Skyla immediately after a first-trimester abortion or miscarriage, unless it is a septic abortion [see Contraindications (4)].
Inserting Skyla after childbirth or second-trimester abortion or miscarriage
Immediate insertion after childbirth or second-trimester abortion or miscarriage | - Insert Skyla after removal of the placenta. Back-up contraception is not needed. [See Contraindications (4), Warnings and Precautions (5.5, 5.6), Adverse Reactions (6.2)].
Interval insertion following complete involution of the uterus | - Wait a minimum of 6 weeks or until the uterus is fully involuted before inserting Skyla [see Warnings and Precautions (5.5, 5.6), Adverse Reactions (6.2)]. - Insert Skyla any time there is reasonable certainty the woman is not pregnant. - If Skyla is not inserted during the first 7 days of the menstrual cycle, a back-up method of contraception should be used, or the woman should abstain from vaginal intercourse for 7 days to prevent pregnancy [see Contraindications (4), Warnings and Precautions (5.2)].

Tools for Insertion

Note: The inserter provided with Skyla (see Figure 1) and the Insertion Procedure described in this section are not applicable for immediate insertion after childbirth or second-trimester abortion or miscarriage. For immediate insertion, remove Skyla from the inserter by first loading (see Figure 2) and then releasing (see Figure 7) Skyla from the inserter, and insert according to accepted practice.

Preparation

- Gloves
- Speculum
- Sterile uterine sound
- Sterile tenaculum
- Antiseptic solution, applicator

Procedure

- Sterile gloves
- Skyla with inserter in sealed package
- Instruments and anesthesia for paracervical block, if anticipated
- Consider having an unopened back-up Skyla available
- Sterile, sharp curved scissors

Preparation for insertion

- Exclude pregnancy and confirm that there are no other contraindications to the use of Skyla.
- Check expiration date of Skyla prior to initiating insertion.
- With the patient comfortably in lithotomy position, do a bimanual exam to establish the size, shape and position of the uterus.
- Gently insert a speculum to visualize the cervix.
- Thoroughly cleanse the cervix and vagina with a suitable antiseptic solution.
- Prepare to sound the uterine cavity. Grasp the upper lip of the cervix with a tenaculum forceps and gently apply traction to stabilize and align the cervical canal with the uterine cavity. Perform a paracervical block if needed. If the uterus is retroverted, it may be more appropriate to grasp the lower lip of the cervix. The tenaculum should remain in position and gentle traction on the cervix should be maintained throughout the insertion procedure.
- Gently insert a uterine sound to check the patency of the cervix, measure the depth of the uterine cavity in centimeters, confirm cavity direction, and detect the presence of any uterine anomaly. If you encounter difficulty or cervical stenosis, use dilatation, and not force, to overcome resistance. If cervical dilatation is required, consider using a paracervical block.

Insertion Procedure

Proceed with insertion only after completing the above steps and ascertaining that the patient is appropriate for Skyla. Ensure use of aseptic technique throughout the entire procedure.

Step 1–Opening of the package

- Open the package (Figure 1). The contents of the package are sterile.

Figure 1. Opening the Skyla Package

- Using sterile gloves, lift the handle of the sterile inserter and remove from the sterile package.

Step 2–Load Skyla into the insertion tube

- Push the slider forward as far as possible in the direction of the arrow, thereby moving the insertion tube over the Skyla T-body to load Skyla into the insertion tube (Figure 2). The tips of the arms will meet to form a rounded end that extends slightly beyond the insertion tube.

Figure 2. Move slider all the way to the forward position to load Skyla

- Maintain forward pressure with your thumb or forefinger on the slider. DO NOT move the slider downward at this time as this may prematurely release the threads of Skyla. Once the slider is moved below the mark, Skyla cannot be re-loaded.

Step 3–Setting the Flange

- Holding the slider in this forward position, set the upper edge of the flange to correspond to the uterine depth (in centimeters) measured during sounding (Figure 3).

Figure 3. Setting the flange

Step 4–Skyla is now ready to be inserted

- Continue holding the slider in this forward position. Advance the inserter through the cervix until the flange is approximately 1.5–2 cm from the cervix and then pause (Figure 4).

Figure 4. Advancing insertion tube until flange is 1.5 to 2 cm from the cervix

Do not force the inserter. If necessary, dilate the cervical canal.

Step 5–Open the arms

- While holding the inserter steady, move the slider down to the mark to release the arms of Skyla (Figure 5). Wait 10 seconds for the horizontal arms to open completely.

Figure 5. Move the slider back to the mark to release and open the arms

Step 6–Advance to fundal position

Advance the inserter gently towards the fundus of the uterus until the flange touches the cervix. If you encounter fundal resistance do not continue to advance. Skyla is now in the fundal position (Figure 6). Fundal positioning of Skyla is important to prevent expulsion.

Figure 6. Move Skyla into the fundal position

Step 7–Release Skyla and withdraw the inserter

- Holding the entire inserter firmly in place, release Skyla by moving the slider all the way down (Figure 7).

Figure 7. Move the slider all the way down to release Skyla from the insertion tube

- Continue to hold the slider all the way down while you slowly and gently withdraw the inserter from the uterus.
- Using a sharp, curved scissor, cut the threads perpendicular, leaving about 3 cm visible outside of the cervix [cutting threads at an angle may leave sharp ends (Figure 8)]. Do not apply tension or pull on the threads when cutting to prevent displacing Skyla.

.

Figure 8. Cutting the threads

Skyla insertion is now complete. Prescribe analgesics, if indicated. Record the Skyla lot number in the patient records.

Important information to consider during or after insertion

- If you suspect that Skyla is not in the correct position, check placement (for example, using transvaginal ultrasound). Remove Skyla if it is not positioned completely within the uterus. Do not reinsert a removed Skyla.
- If there is clinical concern, exceptional pain or bleeding during or after insertion, take appropriate steps (such as physical examination and ultrasound) immediately to exclude perforation.

2.3 Patient Follow-up

Reexamine and evaluate patients 4 to 6 weeks after insertion and once a year thereafter, or more frequently if clinically indicated.

2.4 Removal of Skyla

Timing of Removal

- Skyla should not remain in the uterus after 3 years.
- If pregnancy is not desired, remove Skyla during the first 7 days of the menstrual cycle, provided the woman is still experiencing regular menses. If removal will occur at other times during the cycle or the woman does not experience regular menses, she is at risk of pregnancy, start a new contraceptive method a week prior to removal for these women. [See Dosage and Administration (2.5).]

Tools for Removal

Preparation

- Gloves
- Speculum

Procedure

- Sterile forceps

Removal Procedure

- Remove Skyla by applying gentle traction on the threads with forceps (Figure 9).

Figure 9. Removal of Skyla

- If the threads are not visible, determine location of Skyla by ultrasound [see Warnings and Precautions (5.10)].
- If Skyla is found to be in the uterine cavity on ultrasound exam, it may be removed using a narrow forceps, such as an alligator forceps. This may require dilation of the cervical canal. After removal of Skyla, examine the system to ensure that it is intact. If unable to remove with gentle traction, determine Skyla location and exclude perforation by ultrasound or other imaging [see Warnings and Precautions (5.10)].
- Removal may be associated with some:
  - pain and/or bleeding or vasovagal reactions (for example, syncope, bradycardia) or seizure, especially in patients with a predisposition to these conditions.
  - breakage or embedment of Skyla in the myometrium that can make removal difficult [see Warnings and Precautions (5.5)]. Analgesia, paracervical anesthesia, cervical dilation, alligator forceps or other grasping instrument, or hysteroscopy may be used to assist in removal.

2.5 Continuation of Contraception after Removal

- If pregnancy is not desired and if a woman wishes to continue using Skyla, a new system can be inserted immediately after removal any time during the cycle.
- If a patient with regular cycles wants to start a different contraceptive method, time removal and initiation of the new method to ensure continuous contraception. Either remove Skyla during the first 7 days of the menstrual cycle and start the new method immediately thereafter or start the new method at least 7 days prior to removing Skyla if removal is to occur at other times during the cycle.

If a patient with irregular cycles or amenorrhea wants to start a different contraceptive method, start the new method at least 7 days before removal.

3 DOSAGE FORMS AND STRENGTHS

Skyla is a LNG-releasing IUS (a type of intrauterine device, or IUD) consisting of a T-shaped polyethylene frame with a steroid reservoir containing a total of 13.5 mg LNG.

4 CONTRAINDICATIONS

The use of Skyla is contraindicated when one or more of the following conditions exist:

- Pregnancy or suspicion of pregnancy [see Warnings and Precautions (5.2), Use in Specific Populations (8.1)]
- For use as post-coital contraception (emergency contraception)
- Congenital or acquired uterine anomaly including fibroids, that distorts the uterine cavity
- Acute pelvic inflammatory disease (PID) or a history of PID unless there has been a subsequent intrauterine pregnancy [see Warnings and Precautions (5.4)]
- Postpartum endometritis or infected abortion in the past 3 months
- Known or suspected uterine or cervical malignancy
- Known or suspected breast cancer or other progestin-sensitive cancer, now or in the past
- Uterine bleeding of unknown etiology
- Untreated acute cervicitis or vaginitis, including bacterial vaginosis or other lower genital tract infections until infection is controlled
- Acute liver disease or liver tumor (benign or malignant)
- Conditions associated with increased susceptibility to pelvic infections [see Warnings and Precautions (5.4)]
- A previously inserted intrauterine device (IUD) that has not been removed
- Hypersensitivity to any component of this product [see Adverse Reactions (6.2) and Description (11.1)]

5 WARNINGS AND PRECAUTIONS

5.1 Risk of Ectopic Pregnancy

Evaluate women for ectopic pregnancy if they become pregnant with Skyla in place because the likelihood of a pregnancy being ectopic is increased with Skyla. Approximately one-half of pregnancies that occur with Skyla in place are likely to be ectopic. Also consider the possibility of ectopic pregnancy in the case of lower abdominal pain, especially in association with missed menses or if an amenorrheic woman starts bleeding.

The incidence of ectopic pregnancy in clinical trials with Skyla, which excluded women with a history of ectopic pregnancy, was approximately 0.1% per year. The risk of ectopic pregnancy in women who have a history of ectopic pregnancy and use Skyla is unknown. Women with a previous history of ectopic pregnancy, tubal surgery or pelvic infection carry a higher risk of ectopic pregnancy. Ectopic pregnancy may result in loss of fertility.

5.2 Risks with Intrauterine Pregnancy

If pregnancy occurs while using Skyla, remove Skyla because leaving it in place may increase the risk of spontaneous abortion and preterm labor. Removal of Skyla or probing of the uterus may also result in spontaneous abortion. In the event of an intrauterine pregnancy with Skyla, consider the following:

Septic abortion

In patients becoming pregnant with an IUS in place, septic abortion—with septicemia, septic shock, and death—may occur.

Continuation of pregnancy

If a woman becomes pregnant with Skyla in place and if Skyla cannot be removed or the woman chooses not to have it removed, warn her that failure to remove Skyla increases the risk of miscarriage, sepsis, premature labor and premature delivery. Advise her of isolated reports of virilization of the female fetus following local exposure to LNG during pregnancy with an LNG IUS in place [see Use in Specific Populations (8.1)]. Follow her pregnancy closely and advise her to report immediately any symptom that suggests complications of the pregnancy.

5.3 Sepsis

Severe infection or sepsis, including Group A streptococcal sepsis (GAS), have been reported following insertion of a LNG-releasing IUS. In some cases, severe pain occurred within hours of insertion followed by sepsis within days. Because death from GAS is more likely if treatment is delayed, it is important to be aware of these rare but serious infections. Aseptic technique during insertion of Skyla is essential in order to minimize serious infections such as GAS.

5.4 Pelvic Infection

Pelvic Inflammatory Disease (PID)

Skyla is contraindicated in the presence of known or suspected PID or in women with a history of PID unless there has been a subsequent intrauterine pregnancy [see Contraindications (4)]. IUDs have been associated with an increased risk of PID, most likely due to organisms being introduced into the uterus during insertion. In clinical trials, PID was observed in 0.4% of women overall and occurred more frequently within the first year and most often within the first month after insertion of Skyla.

Promptly examine users with complaints of lower abdominal or pelvic pain, odorous discharge, unexplained bleeding, fever, genital lesions or sores. Remove Skyla in cases of recurrent endometritis or pelvic inflammatory disease, or if an acute pelvic infection is severe or does not respond to treatment.

Women at increased risk for PID

PID is often associated with a sexually transmitted infection (STI), and Skyla does not protect against STI. The risk of PID is greater for women who have multiple sexual partners, and also for women whose sexual partner(s) have multiple sexual partners. Women who have had PID are at increased risk for a recurrence or re-infection. In particular, ascertain whether the woman is at increased risk of infection (for example, leukemia, acquired immune deficiency syndrome [AIDS], intravenous drug abuse).

Subclinical PID

PID may be asymptomatic but still result in tubal damage and its sequelae.

Treatment of PID

Following a diagnosis of PID, or suspected PID, bacteriologic specimens should be obtained, and antibiotic therapy should be initiated promptly. Removal of Skyla after initiation of antibiotic therapy is usually appropriate.

Actinomycosis

Actinomycosis has been associated with IUDs. Remove Skyla from symptomatic women and treat with antibiotics. The significance of actinomyces-like organisms on Pap smear in an asymptomatic IUD user is unknown, and so this finding alone does not always require Skyla removal and treatment. When possible, confirm a Pap smear diagnosis with cultures.

5.5 Perforation

Perforation (total or partial, including penetration/embedment of Skyla in the uterine wall or cervix) may occur most often during insertion, although the perforation may not be detected until sometime later. The incidence of perforation during clinical trials was < 0.1%.

The risk of uterine perforation is increased in women who have recently given birth, and in women who are breastfeeding at the time of insertion. In a large postmarketing safety study conducted in the US, the risk of uterine perforation was highest when insertion occurred within ≤ 6 weeks postpartum, and also higher with breastfeeding at the time of insertion [see Adverse Reactions (6.2)].

The risk of perforation may be increased if Skyla is inserted when the uterus is fixed, retroverted or not completely involuted.

If perforation occurs, locate and remove Skyla. Surgery may be required. Delayed detection or removal of Skyla in case of perforation may result in migration outside the uterine cavity, adhesions, peritonitis, intestinal perforations, intestinal obstruction, abscesses and erosion of adjacent viscera. In addition, perforation may reduce contraceptive efficacy and result in pregnancy.

5.6 Expulsion

Partial or complete expulsion of Skyla may occur resulting in the loss of efficacy. Expulsion may be associated with symptoms of bleeding or pain, or it may be asymptomatic and go unnoticed. Skyla typically decreases menstrual bleeding over time; therefore, an increase of menstrual bleeding may be indicative of an expulsion. Consider further diagnostic imaging, such as x-ray, if expulsion is suspected based on ultrasound [see Warnings and Precautions (5.10)]. In clinical trials, a 3-year expulsion rate of 3.2% (54 out of 1,665 subjects) was reported.

The risk of expulsion is increased with insertions immediately after delivery and appears to be increased with insertion after second-trimester abortion based on limited data. In a large postmarketing safety study conducted in the US, the risk of expulsion was lower with breastfeeding status [see Adverse Reactions (6.2)].

Remove a partially expelled Skyla. If expulsion has occurred, a new Skyla can be inserted any time the provider can be reasonably certain the woman is not pregnant.

5.7 Ovarian Cysts

Because the contraceptive effect of Skyla is mainly due to its local effects within the uterus, ovulatory cycles with follicular rupture usually occur in women of fertile age using Skyla. Ovarian cysts (reported as adverse reactions if they were abnormal, non-functional cysts and/or had a diameter >3 cm on ultrasound examination) were reported at least once over the course of clinical trials in 13.2% of women using Skyla, and 0.3% of subjects discontinued because of an ovarian cyst. Most ovarian cysts are asymptomatic, although some may be accompanied by pelvic pain or dyspareunia. In most cases the ovarian cysts disappear spontaneously during two to three months observation. Evaluate persistent ovarian cysts. Surgical intervention is not usually required.

5.8 Bleeding Pattern Alterations

Skyla can alter the bleeding pattern and result in spotting, irregular bleeding, heavy bleeding, oligomenorrhea and amenorrhea. During the first 3–6 months of Skyla use, the number of bleeding and spotting days may be higher and bleeding patterns may be irregular. Thereafter, the number of bleeding and spotting days usually decreases but bleeding may remain irregular.

In Skyla clinical trials, amenorrhea developed by the end of the first year of use in approximately 6% of Skyla users. A total of 77 subjects out of 1,672 (4.6%) discontinued due to uterine bleeding complaints. Table 2 shows the bleeding patterns as documented in the Skyla clinical trials based on 90-day reference periods. Table 3 shows the number of bleeding and spotting days based on 28-day cycle equivalents.

Table 2: Bleeding Patterns Reported with Skyla in Contraception Studies (by 90-day reference periods)
Skyla | First 90 days N=1,531 | Second 90 days N=1,475 | End of year 1 N=1,329 | End of year 3 N=903
Amenorrhea^1 | <1% | 3% | 6% | 12%
Infrequent bleeding^2 | 8% | 19% | 20% | 22%
Frequent bleeding^3 | 31% | 12% | 8% | 4%
Prolonged bleeding^4 | 55% | 14% | 6% | 2%
Irregular bleeding^5 | 39% | 25% | 18% | 15%

^1Defined as subjects with no bleeding/spotting throughout the 90-day reference period

^2Defined as subjects with 1 or 2 bleeding/spotting episodes in the 90-day reference period

^3Defined as subjects with more than 5 bleeding/spotting episodes in the 90-day reference period

^4Defined as subjects with bleeding/spotting episodes lasting more than 14 days in the 90-day reference period. Subjects with prolonged bleeding may also be included in one of the other categories (excluding amenorrhea)

^5Defined as subjects with 3 to 5 bleeding/spotting episodes and less than 3 bleeding/spotting-free intervals of 14 or more days.

Table 3: Mean number of Bleeding and Spotting Days per 28-day Cycle Equivalent
28-day Cycle Equivalent | Cycle 1; N=1,588 | Cycle 4; N=1,535 | Cycle 7; N=1,468 | Cycle 13; N=1,345 | Cycle 39; N=781
Days on treatment | 1–28 | 85–112 | 169–196 | 337–364 | 1065–1092
 | Mean; (SD) | Mean; (SD) | Mean; (SD) | Mean; (SD) | Mean; (SD)
Number of bleeding days | 7.3; (5.6) | 3.5; (3.4) | 2.8; (3.1) | 2.1; (2.7) | 1.4; (2.1)
Number of spotting days | 9.2; (6.1) | 4.8; (4.4) | 3.8; (3.6) | 3.3; (3.1) | 2.7; (2.7)

If a significant change in bleeding develops during prolonged use, take appropriate diagnostic measures to rule out endometrial pathology. Consider the possibility of pregnancy if menstruation does not occur within six weeks of the onset of a previous menstruation. Once pregnancy has been excluded, repeated pregnancy tests are generally not necessary in amenorrheic women unless indicated, for example, by other signs of pregnancy or by pelvic pain.

5.9 Breast Cancer

Women who currently have or have had breast cancer, or have a suspicion of breast cancer, should not use hormonal contraception, including Skyla because some breast cancers are hormone-sensitive [see Contraindications (4)].

Spontaneous reports of breast cancer have been received during postmarketing experience with a LNG-releasing IUS. Observational studies of the risk of breast cancer with use of a LNG-releasing IUS do not provide conclusive evidence of increased risk.

5.10 Clinical Considerations for Use and Removal

Use Skyla with caution after careful assessment if any of the following conditions exist, and consider removal of the system if any of them arise during use:

- Coagulopathy or use of anticoagulants
- Migraine, focal migraine with asymmetrical visual loss or other symptoms indicating transient cerebral ischemia
- Exceptionally severe headache
- Marked increase of blood pressure
- Severe arterial disease such as stroke or myocardial infarction

In addition, consider removing Skyla if any of the following conditions arise during use:

- Uterine or cervical malignancy
- Jaundice
- If the threads are not visible or are significantly shortened they may have broken or retracted into the cervical canal or uterus. Consider the possibility that the system may have been displaced, (for example, expelled or perforated the uterus) [see Warnings and Precautions (5.5, 5.6)]. Exclude pregnancy and verify the location of Skyla, for example, by sonography, X-ray, or by gentle exploration of the cervical canal with a suitable instrument. If Skyla is displaced, remove it. A new Skyla may be inserted at that time or during the next menses if it is certain that conception has not occurred. If Skyla is in place with no evidence of perforation, no intervention is indicated.

5.11 Magnetic Resonance Imaging (MRI) Safety Information

Non-clinical testing has demonstrated that Skyla is MR Conditional. A patient with Skyla can be safely scanned in an MR system meeting the following conditions:

- Static magnetic field of 3.0 T or less
- Maximum spatial field gradient of 36,000 gauss/cm (360 T/m)
- Maximum MR system reported, whole body averaged specific absorption rate (SAR) of 4W/kg (First Level Controlled Operating Mode)

Under the scan conditions defined above, the Skyla IUS is expected to produce a maximum temperature rise of less than 2°C after 15 minutes of continuous scanning.

In non-clinical testing, the image artifact caused by the IUS extended up to 5 mm from the IUS when imaged with a gradient echo pulse sequence and a 3.0 T MRI system.

6 ADVERSE REACTIONS

The following serious or otherwise important adverse reactions are discussed elsewhere in the labeling:

- Ectopic Pregnancy [see Warnings and Precautions (5.1)]
- Intrauterine Pregnancy [see Warnings and Precautions (5.2)]
- Group A Streptococcal Sepsis (GAS) [see Warnings and Precautions (5.3)]
- Pelvic Inflammatory Disease [see Warnings and Precautions (5.4)]
- Perforation [see Warnings and Precautions (5.5)]
- Expulsion [see Warnings and Precautions (5.6)]
- Ovarian Cysts [see Warnings and Precautions (5.7)]
- Bleeding Pattern Alterations [see Warnings and Precautions (5.8)]

6.1 Clinical Trials Experience

Because clinical trials are conducted under widely varying conditions, adverse reaction rates observed in the clinical trials of a drug cannot be directly compared to rates in the clinical trials of another drug and may not reflect the rates observed in clinical practice.

The data described below reflect exposure to Skyla in 1,672 patients in two contraception studies, including 1,383 exposed for one year and 993 who completed the three year studies. The population was generally healthy, 18 to 40-year old females requesting contraception and predominately Caucasian (82.6%). The data cover more than 40,000 cycles of exposure. The frequencies of reported adverse drug reactions represent crude incidences.

Most common adverse reactions (occurring in ≥ 5% users) were increased bleeding (7.8%), vulvovaginitis (20.2%), abdominal/pelvic pain (18.9%), acne/seborrhea (15.0%), ovarian cyst (13.2%), headache (12.4%), dysmenorrhea (8.6%), breast pain/discomfort (8.6%) and nausea (5.5%).

In the contraception studies, 18% discontinued prematurely due to an adverse reaction. The most common adverse reactions leading to discontinuation (in >1% of users) were uterine bleeding complaints (4.6%), device expulsion (3.2%), acne/seborrhea (2.9%), abdominal pain (2.5%) dysmenorrhea/uterine spasms (2.0%) and pelvic pain (1.8%).

Other common adverse reactions (occurring in ≥ 1% users) by System Organ Class (SOC): The frequencies of adverse reactions observed in clinical trials are summarized in Table 4 by SOC (presented as crude incidences).

Table 4: Adverse reactions that occurred in at least 1% of Skyla users in clinical trials by SOC
System Organ Class | Adverse Reaction | Incidence (%) (N=1,672)
Reproductive System and Breast Disorders | Vulvovaginitis | 20.2
 | Ovarian cyst [Ovarian cysts were reported as adverse events if they were abnormal, non-functional cysts and/or had a diameter >3 cm on ultrasound examination] | 13.2
 | Dysmenorrhea | 8.6
 | Increased bleeding [Not all bleeding alterations were captured as adverse reactions [see Warnings and Precautions (5.8)].] | 7.8
 | Breast pain/discomfort | 5.3/3.3
 | Genital discharge | 4.2
 | Device expulsion (complete and partial) | 3.2
 | Upper genital tract infection | 1.4
Gastrointestinal Disorders | Abdominal pain/pelvic pain | 12.7/6.2
 | Nausea | 5.5
Skin and Subcutaneous Tissue Disorders | Acne/Seborrhea | 13.6/1.4
 | Alopecia | 1.2
Nervous System Disorders | Headache | 12.4
 | Migraine | 2.3
Psychiatric Disorders | Depression/Depressed mood | 3.8/0.5

6.2 Postmarketing Experience

Adverse Reactions from Postmarketing Spontaneous Reports

The following adverse reactions have been identified during post-approval use of LNG-releasing IUSs. Because these reactions are reported voluntarily from a population of uncertain size, it is not always possible to reliably estimate their frequency or establish a causal relationship to drug exposure.

- Arterial thrombotic and venous thromboembolic events, including cases of pulmonary embolism, deep vein thrombosis and stroke
- Device breakage
- Hypersensitivity (including rash, urticaria, and angioedema)
- Increased blood pressure

Reported Adverse Reactions from Postmarketing Studies

Assessment of Perforation and Expulsion of Intrauterine Devices (APEX IUD) Study

APEX IUD was a large US retrospective cohort study to assess the impact of breastfeeding and timing of postpartum IUD insertion on uterine perforation and IUD expulsion. The analyses included a total of 326,658 insertions, 30% (97,824 insertions) of which were performed in women with a delivery in the previous 12 months. For insertions performed in women who had delivered ≤ 52 weeks before IUD insertion, the majority of postpartum insertions, 57.3% (56,047 insertions) occurred between 6 and 14 weeks postpartum. Breastfeeding data were available in 94,817 insertions performed in women 52 weeks or less after delivery.

The study results indicated that the risk of uterine perforation was highest in women with IUD insertion ≤ 6 weeks postpartum. Immediate postpartum insertion (0–3 days) findings are limited due to the relatively small number of insertions occurring within this time interval. Women who were breastfeeding at the time of insertion were at 33% higher risk of perforation (adjusted hazard ratio [HR]=1.33, 95% confidence interval [CI]: 1.07–1.64) compared to women who were not breastfeeding at the time of insertion. Progressively lower risk of uterine perforation was observed in postpartum time windows beyond 6 weeks, in both breastfeeding and not breastfeeding women. Table 5 presents the uterine perforation rates for LNG IUS stratified by breastfeeding status and postpartum interval.

Table 5: Uterine Perforation1 rates for LNG IUS, by Breastfeeding Status and Postpartum Interval
 | Breastfeeding at time of insertion |  | Not breastfeeding at time of insertion
Postpartum interval at time of insertion | Number of events/ insertions | Uterine perforation rate per 1,000 insertions | Number of events/ insertions | Uterine perforation rate per 1,000 insertions
0 to 3 days | 8/1,896 | 4.22 | 0/277 | 0.00
4 days to ≤ 6 weeks | 120/10,735 | 11.18 | 28/2,377 | 11.78
> 6 to ≤ 14 weeks | 268/29,677 | 9.03 | 80/12,011 | 6.66
> 14 to ≤ 52 weeks | 43/6,139 | 7.00 | 22/9,089 | 2.42
> 52 weeks or no delivery | no data available |  | 243/184,733 | 1.32

^1Uterine perforation includes both complete and partialperforation

Risk of expulsion was variable over the postpartum intervals through 52 weeks. Women who were breastfeeding were at 28% lower risk of IUD expulsion (adjusted HR=0.72, 95% CI: 0.64-0.80) compared to women who were not breastfeeding at time of insertion. Table 6 presents the IUD expulsion rates for LNG IUS stratified by breastfeeding status and postpartum interval.

Table 6: Expulsion1 Rates for LNG IUS, by Breastfeeding Status and Postpartum Interval
 | Breastfeeding at time of insertion |  | Not breastfeeding at time of insertion
Postpartum interval at time of insertion | Number of events/ insertions | Expulsion rate per 1,000 insertions | Number of events/ insertions | Expulsion rate per 1,000 insertions
0 to 3 days | 187/1,896 | 98.63 | 12/277 | 43.32
4 days to ≤ 6 weeks | 185/10,735 | 17.23 | 52/2,377 | 21.88
> 6 to ≤ 14 weeks | 421/29,677 | 14.19 | 306/12,011 | 25.48
> 14 to ≤ 52 weeks | 120/6,139 | 19.55 | 273/9,089 | 30.04
> 52 weeks or no delivery | no data available |  | 5,481/184,733 | 29.67

^1Expulsion includes both complete and partial expulsion

7 DRUG INTERACTIONS

No drug-drug interaction studies have been conducted with Skyla.

Drugs or herbal products that induce or inhibit LNG metabolizing enzymes, including CYP3A4, may decrease or increase, respectively, the serum concentrations of LNG during the use of Skyla. However, the contraceptive effect of Skyla is mediated via the direct release of LNG into the uterine cavity and is unlikely to be affected by drug interactions via enzyme induction or inhibition.

8 USE IN SPECIFIC POPULATIONS

8.1 Pregnancy

Risk Summary

The use of Skyla is contraindicated in pregnancy or with a suspected pregnancy and Skyla may cause adverse pregnancy outcomes [see Contraindications (4), Warnings and Precautions (5.1, 5.2)]. If a woman becomes pregnant with Skyla in place, the likelihood of ectopic pregnancy is increased and there is an increased risk of miscarriage, sepsis, premature labor, and premature delivery. Remove Skyla, if possible, if pregnancy occurs in a woman using Skyla. If Skyla cannot be removed, follow the pregnancy closely [see Warnings and Precautions (5.1, 5.2)].

There have been isolated cases of virilization of the external genitalia of the female fetus following local exposure to LNG during pregnancy with an LNG IUS in place. Animal reproduction studies have not been conducted with Skyla.

8.2 Lactation

Risk Summary

Published studies report the presence of LNG in human milk. Small amounts of progestins (approximately 0.1% of the total maternal doses) were detected in the breast milk of nursing mothers who used other LNG-releasing IUSs, resulting in exposure of LNG to the breastfed infants. There are no reports of adverse effects in breastfed infants with maternal use of progestin-only contraceptives. Isolated cases of decreased milk production have been reported with a LNG-releasing IUS. The developmental and health benefits of breastfeeding should be considered along with the mother’s clinical need for Skyla and any potential adverse effects on the breastfed child from Skyla or from the underlying maternal condition.

8.3 Females and Males of Reproductive Potential

Return to Fertility After Discontinuing Skyla

About 77% of women who desired pregnancy after study discontinuation and provided follow-up information, conceived within 12 months after removal of Skyla.

8.4 Pediatric Use

Safety and efficacy of Skyla have been established in women of reproductive age. Efficacy is expected to be the same for postpubertal females under the age of 18 as for users 18 years and older. Use of this product before menarche is not indicated.

8.5 Geriatric Use

Skyla has not been studied in women over age 65 and is not approved for use in this population.

11 DESCRIPTION

Skyla (levonorgestrel-releasing intrauterine system) contains 13.5 mg of LNG, a progestin, and is intended to provide an initial release rate of approximately14 mcg/day of LNG after 24 days.

Levonorgestrel USP, (-)-13-Ethyl-17-hydroxy-18,19-dinor-17α-pregn-4-en-20-yn-3-one, the active ingredient in Skyla, has a molecular weight of 312.4, a molecular formula of C21H28O2, and the following structural formula:

11.1 Skyla

Skyla consists of a T-shaped polyethylene frame (T-body) with a steroid reservoir (hormone elastomer core) around the vertical stem. The white T-body has a loop at one end of the vertical stem and two horizontal arms at the other end. The reservoir consists of a whitish or pale yellow cylinder, made of a mixture of LNG and silicone (polydimethylsiloxane), containing a total of 13.5 mg LNG. The reservoir is covered by a semi-opaque silicone membrane, composed of polydimethylsiloxane and colloidal silica. A ring composed of 99.95% pure silver is located at the top of the vertical stem close to the horizontal arms and is visible by ultrasound. The polyethylene of the T-body is compounded with barium sulfate, which makes it radiopaque. A monofilament brown polyethylene removal thread is attached to a loop at the end of the vertical stem of the T-body. The polyethylene of the removal thread contains iron oxide as a colorant (see Figure 10).

The components of Skyla, including its packaging, are not manufactured using natural rubber latex.

Figure 10. Skyla

11.2 Inserter

Skyla is packaged sterile within an inserter. The inserter (Figure 11), which is used for insertion of Skyla into the uterine cavity, consists of a symmetric two-sided body and slider that are integrated with flange, lock, pre-bent insertion tube and plunger. The outer diameter of the insertion tube is 3.8 mm. The vertical stem of Skyla is loaded in the insertion tube at the tip of the inserter. The arms are pre-aligned in the horizontal position. The removal threads are contained within the insertion tube and handle. Once Skyla has been placed, the inserter is discarded.

Figure 11. Diagram of Inserter

12 CLINICAL PHARMACOLOGY

12.1 Mechanism of Action

The local mechanism by which continuously released LNG contributes to the contraceptive effectiveness of Skyla has not been conclusively demonstrated. Studies of Skyla and similar LNG IUS prototypes have suggested several mechanisms that prevent pregnancy: thickening of cervical mucus preventing passage of sperm into the uterus, inhibition of sperm capacitation or survival, and alteration of the endometrium.

12.2 Pharmacodynamics

Skyla has mainly local progestogenic effects in the uterine cavity. The local concentrations of LNG lead to morphological changes including stromal pseudodecidualization, glandular atrophy, a leukocytic infiltration and a decrease in glandular and stromal mitoses.

In clinical trials with Skyla, ovulation was assessed based on serum progesterone values >2.5 ng/mL in one study and serum progesterone values >2.5 ng/mL together with serum estradiol levels <27.24 pg/mL in another study. Evidence of ovulation by these criteria was seen in 34 out of 35 women in the first year, in 26 out of 27 women in the second year, and in all 26 women in the third year.

12.3 Pharmacokinetics

Absorption

Low doses of LNG are administered into the uterine cavity with the Skyla intrauterine delivery system. The in vivo release rate is approximately 14 mcg/day after 24 days and is reduced to approximately 10 mcg/day after 60 days and then declines progressively to approximately 6 mcg/day after 1 year and 5 mcg/day after 3 years. The average LNG in vivo release rate is approximately 8 mcg/day over the first year of use and 6 mcg/day over the period of 3 years.

In a subset of 7 subjects, the maximum observed serum LNG concentration (mean ±SD) was 192 ± 105 pg/mL, reached after 2 days (median) of Skyla insertion. Thereafter, the LNG serum concentrations (mean ±SD) at year 1, 2, and 3 were 77 ± 21 pg/mL, 62 ± 38 pg/mL, and 72 ± 29 pg/mL, respectively. A population pharmacokinetic evaluation based on a broader database (>1000 patients) showed similar concentration data of 168 ± 46 pg/mL at 7 days after placement. Thereafter, LNG serum concentrations decline slowly to a value 61 ± 19 pg/mL after 3 years.

Distribution

The apparent volume of distribution of LNG is reported to be approximately 1.8 L/kg. LNG is bound non-specifically to serum albumin and specifically to sex hormone binding globulin (SHBG). Accordingly, changes in the concentration of SHBG in serum result in an increase (at higher SHBG concentration) or a decrease (at lower SHBG concentration) of the total LNG concentration in serum. In a subset of 7 subjects, the concentration of SHBG declined by a mean value of 18% within 2 weeks after insertion of Skyla and remained relatively stable over the 3 year period of use. Less than 2% of the circulating LNG is present as free steroid.

Elimination

Following intravenous administration of 0.09 mg LNG to healthy volunteers, the total clearance of LNG is approximately 1 mL/min/kg and the elimination half-life is approximately 20 hours. Metabolic clearance rates may differ among individuals by several-fold, and this may account in part for wide individual variations in LNG concentrations seen in individuals using LNG–containing contraceptive products.

Metabolism

Following absorption, LNG is extensively metabolized. The most important metabolic pathways are the reduction of the Δ4-3-oxo group and hydroxylations at positions 2α, 1β and 16β, followed by conjugation. Significant amounts of conjugated and unconjugated 3α, 5β- are also present in serum, along with much smaller amounts of 3α, 5α-tetrahydrolevonorgestrel and 16β-hydroxylevonorgestrel. CYP3A4 is the main enzyme involved in the oxidative metabolism of LNG.

Excretion

LNG and its phase I metabolites are excreted primarily as glucuronide conjugates. About 45% of LNG and its metabolites are excreted in the urine and about 32% are excreted in feces, mostly as glucuronide conjugates.

Specific Populations

Pediatric: Safety and efficacy of Skyla have been established in women of reproductive age. Use of this product before menarche is not indicated.

In a one-year phase 3 study in post-menarcheal female adolescents (mean age 16.2, range 12 to 18 years) using Skyla, the population pharmacokinetic analysis of 278 adolescents showed mean estimated LNG serum concentrations slightly higher (approximately 10%) in adolescents compared to prior data in adults. This correlates to the generally lower body weight in adolescents. The ranges estimated for adolescents lie within the ranges estimated for adults.

Geriatric: Skyla has not been studied in women over age 65 and is not approved for use in this population.

Race: A three-year phase 3 study in the Asian-Pacific region (93% Asian women, the majority of whom were Chinese, 7% other ethnicities) using Skyla was performed. The population pharmacokinetic analysis of the Asian (Chinese) population in this study showed that estimated LNG serum concentrations in Asian women were slightly higher (approximately 4 to 16%) than those in another phase 3 study which was performed in mainly Caucasian women (79.7%). This slightly higher exposure might be explained by the lower body weight of Asian women.

Hepatic Impairment: No studies were conducted to evaluate the effect of hepatic disease on the disposition of Skyla.

Renal Impairment: No formal studies were conducted to evaluate the effect of renal disease on the disposition of Skyla.

Drug-Drug Interactions

No drug-drug interaction studies were conducted with Skyla [see Drug Interactions (7)].

13 NONCLINICAL TOXICOLOGY

13.1 Carcinogenesis, Mutagenesis, Impairment of Fertility

[See Warnings and Precautions (5.9).]

14 CLINICAL STUDIES

The contraceptive efficacy of Skyla was evaluated in a clinical trial that enrolled generally healthy women aged 18–35, 1,432 of whom received Skyla. Of these, 38.8 % (556) were nulliparous women, and 819 women completed 3 years of use. The trial was a multicenter, multi-national, randomized open-label study conducted in 11 countries in Europe, Latin America, the US and Canada. Women less than six weeks postpartum, with a history of ectopic pregnancy, with clinically significant ovarian cysts or with HIV or otherwise at high risk for sexually transmitted infections were excluded. A total of 540 (37.7%) were treated at US sites and 892 (62.3%) were at non-US sites. The racial demographics of enrolled women who received Skyla was: Caucasian (79.7%), Hispanic (11.5%), Black/African Americans (5.2%), Other (2.7%) and Asian (0.8%). The weight range was 38 to 155 kg (mean weight: 68.7 kg) and mean BMI was 25.3 kg/m^2 (range 16–55 kg/m^2). The clinical trial had no upper or lower weight or BMI limit. Of Skyla-treated women, 21.9% discontinued the study treatment due to an adverse event, 4.4% were lost to follow up, 1.8% withdrew for unspecified reasons, 1.1% discontinued due to protocol deviation, 0.6% discontinued due to pregnancy, and 13.0% discontinued due to other reasons.

The pregnancy rate calculated as the Pearl Index (PI) in women aged 18–35 years was the primary efficacy endpoint used to assess contraceptive reliability. The PI was calculated based on 28-day equivalent exposure cycles; evaluable cycles excluded those in which back-up contraception was used unless a pregnancy occurred in that cycle. Skyla-treated women provided 15,763 evaluable 28-day cycle equivalents in the first year and 39,368 evaluable cycles over the three year treatment period. The PI estimate for the first year of use based on the 5 pregnancies that occurred after the onset of treatment and within 7 days after Skyla removal or expulsion was 0.41 with a 95% upper confidence limit of 0.96. The cumulative 3-year pregnancy rate, based on 10 pregnancies, estimated by the Kaplan-Meier method was 0.9 per 100 women or 0.9%, with a 95% upper confidence limit of 1.7%.

15 REFERENCES

^1 http://www.cdc.gov/std/tg2015/pid.htm. Accessed August 22, 2016.

16 HOW SUPPLIED/STORAGE AND HANDLING

Skyla (levonorgestrel-releasing intrauterine system), containing a total of 13.5 mg LNG, is available in a carton of one sterile unit. NDC# 50419-422-01

Skyla is supplied sterile. Skyla is sterilized with ethylene oxide. Do not resterilize. For single use only. Do not use if the inner package is damaged or open. Insert before the end of the month shown on the label.

Store at 25°C (77°F); with excursions permitted between 15–30°C (59–86°F) [see USP Controlled Room Temperature].

17 PATIENT COUNSELING INFORMATION

Advise the patient to read the FDA-approved patient labeling (Patient Information)

- Sexually Transmitted Infections: Advise the patient that this product does not protect against HIV infection (AIDS) and other sexually transmitted infections (STIs).
- Risk of Ectopic Pregnancy: Advise the patient about the risks of ectopic pregnancy, including the loss of fertility. Teach her to recognize and report to her healthcare provider promptly any symptoms of ectopic pregnancy. [See Warnings and Precautions (5.1).]
- Risks of Intrauterine Pregnancy: Advise the patient to contact her healthcare provider if she thinks she might be pregnant. Inform the patient about the risks of intrauterine pregnancy while using Skyla, including the risks of leaving Skyla in place and the risks of removing Skyla or probing of the uterus. If Skyla cannot be removed in a pregnant patient, advise her to report immediately any symptom that suggests complications of the pregnancy. Advise her of isolated reports of virilization of the female fetus following local exposure to LNG during pregnancy with an LNG IUS in place. [See Warnings and Precautions (5.2) and Use in Special Populations (8.1).]
- Sepsis: Advise the patient that severe infection or sepsis, including Group A streptococcal sepsis (GAS), can occur within the first few days after Skyla is inserted. Instruct her to contact a healthcare provider immediately if she develops severe pain or fever shortly after Skyla is inserted. [See Warnings and Precautions (5.3).]
- Pelvic Infection: Advise the patient about the possibility of pelvic infections including PID and that these infections can cause tubal damage leading to ectopic pregnancy or infertility, or infrequently can necessitate hysterectomy, or cause death. Teach patients to recognize and report to their healthcare provider promptly any symptoms of pelvic infection. These symptoms include development of menstrual disorders (prolonged or heavy bleeding), unusual vaginal discharge, abdominal or pelvic pain or tenderness, dyspareunia, chills, and fever. [See Warnings and Precautions (5.4).]
- Perforation and Expulsion: Advise the patient that the IUS may be expelled from or perforate the uterus and instruct her on how she can check that the threads still protrude from the cervix. Inform her that excessive pain or vaginal bleeding during Skyla placement, worsening pain or bleeding after placement, or the inability to feel Skyla strings may occur with Skyla perforation and expulsion. Caution her not to pull on the threads and displace Skyla. Inform her that there is no contraceptive protection if Skyla is displaced or expelled. Instruct the patient to contact her healthcare provider if she cannot feel the threads and to avoid intercourse or use a non-hormonal back-up birth control (such as condoms or spermicide) until the location of Skyla has been confirmed. Advise her that if perforation occurs, Skyla will have to be located and removed; surgery may be required. [See Warnings and Precautions (5.5, 5.6, 5.10).]
- Ovarian Cysts: Advise the patient regarding the risk of ovarian cysts and that cysts can cause clinical symptoms including pelvic pain, abdominal pain or dyspareunia. Advise the patient to contact her healthcare provider if she experiences these symptoms. [See Warnings and Precautions (5.7).]
- Bleeding Pattern Alterations: Advise the patient that irregular or prolonged bleeding and spotting, and/or cramps may occur during the first few weeks after insertion. Inform the patient that, during the first 3–6 months of Skyla use, the number of bleeding and spotting days may be higher and bleeding patterns may be irregular. If her symptoms continue or are severe she should report them to her healthcare provider. [See Warnings and Precautions (5.8).]
- Clinical Considerations for Use and Removal: Advise the patient to contact her healthcare provider if she experiences any of the following:
- A stroke or heart attack
- Very severe or migraine headaches
- Unexplained fever
- Yellowing of the skin or whites of the eyes, as these may be signs of serious liver problems
- Pregnancy or suspected pregnancy
- Pelvic pain, abdominal pain, or pain during sex
- HIV positive seroconversion in herself or her partner
- Possible exposure to STIs
- Unusual vaginal discharge or genital sores
- Severe vaginal bleeding or bleeding that lasts a long time, or if she misses a menstrual period
- Inability to feel Skyla's threads
- Magnetic Resonance Imaging (MRI) Safety Information: Inform the patient that Skyla can be safely scanned with MRI only under specific conditions [see Warnings and Precautions (5.11)]. Instruct patients who will have an MRI to tell their doctor that they have Skyla.

Manufactured for:

Bayer HealthCare Pharmaceuticals Inc.
Whippany, NJ 07981

© 2013, Bayer HealthCare Pharmaceuticals Inc.
All rights reserved.

Patient Information

Skyla (sky-lah)

(levonorgestrel-releasing intrauterine system)

Read this Patient Information carefully before you decide if Skyla is right for you. This information does not take the place of talking with your gynecologist or other healthcare provider who specializes in women’s health. If you have any questions about Skyla, ask your healthcare provider. You should also learn about other birth control methods to choose the one that is best for you.

Skyla does not protect against HIV infection (AIDS) and other sexually transmitted infections (STIs).

What is Skyla?

- Skyla is a hormone-releasing system placed in your uterus by your healthcare provider to prevent pregnancy for up to 3 years.
- Skyla can be removed by your healthcare provider at any time.
- Skyla can be used whether or not you have given birth to a child.

Skyla is a small, flexible plastic T-shaped system that slowly releases a progestin hormone called levonorgestrel (LNG) that is often used in birth control pills. Because Skyla releases LNG into your uterus, only small amounts of the hormone enter your blood. Skyla does not contain estrogen.

Two thin threads are attached to the stem (lower end) of Skyla. The threads are the only part of Skyla you can feel when Skyla is in your uterus; however, unlike a tampon string, the threads do not extend outside your body.

Skyla is small

and flexible

What if I need birth control for more than 3 years?

Skyla must be removed after 3 years. Your healthcare provider can place a new Skyla during the same office visit if you choose to continue using Skyla.

What if I want to stop using Skyla?

Skyla is intended for use up to 3 years but you can stop using Skyla at any time by asking your healthcare provider to remove it. You could become pregnant as soon as Skyla is removed, so you should use another method of birth control if you do not want to become pregnant. Talk to your healthcare provider about the best birth control methods for you, because your new method may need to be started 7 days before Skyla is removed to prevent pregnancy.

What if I change my mind about birth control and want to become pregnant in less than 3 years?

Your healthcare provider can remove Skyla at any time. You may become pregnant as soon as Skyla is removed. About 3 out of 4 women who want to become pregnant will become pregnant sometime in the first year after Skyla is removed.

How does Skyla work?

Skyla may work in several ways including thickening cervical mucus, inhibiting sperm movement, reducing sperm survival, and thinning the lining of your uterus. It is not known exactly how these actions work together to prevent pregnancy.

How well does Skyla work for contraception?

The following chart shows the chance of getting pregnant for women who use different methods of birth control. Each box on the chart contains a list of birth control methods that are similar in effectiveness. The most effective methods are at the top of the chart. The box on the bottom of the chart shows the chance of getting pregnant for women who do not use birth control and are trying to get pregnant.

Skyla, an intrauterine device (IUD) also known as an intrauterine system (IUS),, is in the box at the top of the chart.

Who might use Skyla?

You might choose Skyla if you:

- want long-term birth control that provides a low chance of getting pregnant (less than 1 in 100)
- want birth control that works continuously for up to 3 years
- want birth control that is reversible
- want a birth control method that you do not need to take daily
- are willing to use a birth control method that is placed in the uterus
- want birth control that does not contain estrogen

Do not use Skyla if you:

- are or might be pregnant; Skyla cannot be used as an emergency contraceptive
- have a serious pelvic infection called pelvic inflammatory disease (PID) or have had PID in the past unless you have had a normal pregnancy after the infection went away
- have an untreated genital infection now
- have had a serious pelvic infection in the past 3 months after a pregnancy
- can get infections easily. For example, if you:
- have multiple sexual partners or your partner has multiple sexual partners
- have problems with your immune system
- use or abuse intravenous drugs
- have or suspect you might have cancer of the uterus or cervix
- have bleeding from the vagina that has not been explained
- have liver disease or a liver tumor
- have breast cancer or any other cancer that is sensitive to progestin (a female hormone), now or in the past
- have an intrauterine device in your uterus already
- have a condition of the uterus that changes the shape of the uterine cavity, such as large fibroid tumors
- are allergic to levonorgestrel, silicone, polyethylene, silver, silica, barium sulfate or iron oxide

Before having Skyla placed, tell your healthcare provider about all of your medical conditions including if you:

- have any of the conditions listed above
- have had a heart attack
- have had a stroke
- were born with heart disease or have problems with your heart valves
- have problems with blood clotting or take medicine to reduce clotting
- have high blood pressure
- recently had a baby or are breastfeeding
- have severe headaches or migraine headaches
- have AIDS, HIV, or any other sexually transmitted infection

Tell your healthcare provider about all of the medicines you take, including prescription and over-the-counter medicines, vitamins, and herbal supplements.

How is Skyla placed?

Skyla is placed by your healthcare provider during an in-office visit or immediately after giving birth.

First, your healthcare provider will examine your pelvis to find the exact position of your uterus. Your healthcare provider will then clean your vagina and cervix with an antiseptic solution and slide a slim plastic tube containing Skyla through the cervix into your uterus. Your healthcare provider will then remove the plastic tube, and leave Skyla in your uterus. Your healthcare provider will cut the threads to the right length.

You may experience pain, bleeding or dizziness during and after placement. If your symptoms do not pass within 30 minutes after placement, Skyla may not have been placed correctly. Your healthcare provider will examine you to see if Skyla needs to be removed or replaced.

Should I check that Skyla is in place?

Yes, you should check that Skyla is in proper position by feeling the removal threads. It is a good habit to do this 1 time a month. Your healthcare provider should teach you how to check that Skyla is in place. First, wash your hands with soap and water. You can check by reaching up to the top of your vagina with clean fingers to feel the removal threads. Do not pull on the threads. If you feel more than just the threads or if you cannot feel the threads, Skyla may not be in the right position and may not prevent pregnancy. Avoid intercourse or use non-hormonal back-up birth control (such as condoms or spermicide) and ask your healthcare provider to check that Skyla is still in the right place.

How soon after placement of Skyla should I return to my healthcare provider?

Call your healthcare provider if you have any questions or concerns (see “When should I call my healthcare provider?”). Otherwise, you should return to your healthcare provider for a follow-up visit 4 to 6 weeks after Skyla is placed to make sure that Skyla is in the right position.

Can I use tampons or menstrual cups with Skyla?

Yes, tampons or menstrual cups may be used with Skyla. Change tampons or menstrual cups with care to avoid pulling the threads of Skyla. If you think you may have pulled Skyla out of place, avoid intercourse or use a non-hormonal back-up birth control (such as condoms or spermicide), and contact your healthcare provider.

What if I become pregnant while using Skyla?

Call your healthcare provider right away if you think you may be pregnant. If possible, also do a urine pregnancy test. If you get pregnant while using Skyla, you may have an ectopic pregnancy. This means that the pregnancy is not in the uterus. Unusual vaginal bleeding or abdominal pain may be a sign of ectopic pregnancy.

Ectopic pregnancy is a medical emergency that often requires surgery. Ectopic pregnancy can cause internal bleeding, infertility, and even death.

There are also risks if you get pregnant while using Skyla and the pregnancy is in the uterus. Severe infection, miscarriage, premature delivery, and even death can occur with pregnancies that continue with an intrauterine device (IUD). Because of this, your healthcare provider may try to remove Skyla, even though removing it may cause a miscarriage. If Skyla cannot be removed, talk with your healthcare provider about the benefits and risks of continuing the pregnancy and possible effects of the hormone on your unborn baby.

If you continue your pregnancy, see your healthcare provider regularly. Call your healthcare provider right away if you get flu-like symptoms, fever, chills, cramping, pain, bleeding, vaginal discharge, or fluid leaking from your vagina. These may be signs of infection.

How will Skyla change my periods?

For the first 3 to 6 months, your period may become irregular and the number of bleeding days may increase. You may also have frequent spotting or light bleeding. Some women have heavy bleeding during this time. You may also have cramping during the first few weeks. After you have used Skyla for a while, the number of bleeding and spotting days is likely to lessen. For some women, periods will stop altogether. When Skyla is removed, your menstrual periods should return.

Is it safe to breastfeed while using Skyla?

You may use Skyla when you are breastfeeding. Skyla is not likely to affect the quality or amount of your breast milk or the health of your nursing baby. However, isolated cases of decreased milk production have been reported. The risk of Skyla going into the wall of the uterus (becoming embedded) or going through the wall of the uterus is increased if Skyla is inserted while you are breastfeeding.

Will Skyla interfere with sexual intercourse?

You and your partner should not feel Skyla during intercourse. Skyla is placed in the uterus, not in the vagina. Sometimes your partner may feel the threads. If this occurs, or if you or your partner experience pain during sex, talk with your healthcare provider.

Can I have an MRI with Skyla in place?

Skyla can be safely scanned with MRI only under specific conditions. Before you have an MRI, tell your healthcare provider that you have Skyla, an intrauterine device (IUD), in place.

What are the possible side effects of Skyla?

Skyla can cause serious side effects, including:

- Ectopic pregnancy and intrauterine pregnancy risks. There are risks if you become pregnant while using Skyla (see “What if I become pregnant while using Skyla?”).
- Life-threatening infection. Life-threatening infection can occur within the first few days after Skyla is placed. Call your healthcare provider immediately if you develop severe pain or fever shortly after Skyla is placed.
- Pelvic inflammatory disease (PID). Some IUD users get a serious pelvic infection called pelvic inflammatory disease. PID is usually sexually transmitted. You have a higher chance of getting PID if you or your partner has sex with other partners. PID can cause serious problems such as infertility, ectopic pregnancy or pelvic pain that does not go away. PID is usually treated with antibiotics. More serious cases of PID may require surgery including removal of the uterus (hysterectomy). In rare cases, infections that start as PID can even cause death.
Tell your healthcare provider right away if you have any of these signs of PID: long-lasting or heavy bleeding, unusual vaginal discharge, low abdominal (stomach area) pain, painful sex, chills, fever, genital lesions or sores.
- Perforation. Skyla may go into the wall of the uterus (become embedded) or go through the wall of the uterus. This is called perforation. If this occurs, Skyla may no longer prevent pregnancy. If perforation occurs, Skyla may move outside the uterus and can cause internal scarring, infection, or damage to other organs, and you may need surgery to have Skyla removed. Excessive pain or vaginal bleeding during placement of Skyla, pain or bleeding that gets worse after placement, or not being able to feel the threads may happen with perforation. The risk of perforation is increased if Skyla is inserted while you are breastfeeding, or if you have recently given birth.
- Expulsion. Skyla may come out by itself. This is called expulsion. Expulsion occurs in about 3 out of 100 women. Excessive pain or vaginal bleeding during placement of Skyla, pain or bleeding that gets worse after placement, or not being able to feel the threads may happen with expulsion. You may become pregnant if Skyla comes out. If you think that Skyla has come out, avoid intercourse or use a non-hormonal backup birth control (such as condoms or spermicide) and call your healthcare provider. The risk of expulsion is increased with insertion right after delivery or second-trimester abortion.

Common side effects of Skyla include:

- Pain, bleeding or dizziness during and after placement. If these symptoms do not stop 30 minutes after placement, Skyla may not have been placed correctly. Your healthcare provider will examine you to see if Skyla needs to be removed or replaced.
- Changes in bleeding. You may have bleeding and spotting between menstrual periods, especially during the first 3–6 months. Sometimes the bleeding is heavier than usual at first. However, the bleeding usually becomes lighter than usual and may be irregular. Call your healthcare provider if the bleeding remains heavier than usual or increases after it has been light for a while.
- Missed menstrual periods. About 1 out of 16 women stop having periods after 1 year of Skyla use. If you have any concerns that you may be pregnant while using Skyla, do a urine pregnancy test and call your healthcare provider. If you do not have a period for 6 weeks during Skyla use, call your healthcare provider. When Skyla is removed, your menstrual periods should return.
- Cysts on the ovary. About 14 out of 100 women using Skyla develop a cyst on the ovary. These cysts usually disappear on their own in two to three months. However, cysts can cause pain and sometimes cysts will need surgery.

Other common side effects include:

- abdominal or pelvic pain
- acne or greasy skin
- headache or migraine
- inflammation or infection of the outer part of your vagina (vulvovaginitis)
- painful periods

These are not all of the possible side effects with Skyla. For more information, ask your healthcare provider.

Call your doctor for medical advice about side effects. You may report side effects to FDA at 1-800-FDA-1088.

You may also report side effects to Bayer Healthcare Pharmaceuticals at 1-888-842-2937.

After Skyla has been placed, when should I call my healthcare provider?

If Skyla is accidentally removed and you had vaginal intercourse within the preceding week, you may be at risk of pregnancy, and you should talk to a healthcare provider.

Call your healthcare provider if you have any concerns about Skyla. Be sure to call if you:

- think you are pregnant
- have pelvic pain, abdominal pain, or pain during sex
- have unusual vaginal discharge or genital sores
- have unexplained fever, flu-like symptoms or chills
- might be exposed to sexually transmitted infections (STIs)
- are concerned that Skyla may have been expelled (came out)
- cannot feel Skyla's threads
- develop very severe or migraine headaches
- have yellowing of the skin or whites of the eyes. These may be signs of liver problems.
- have had a stroke or heart attack
- become HIV positive or your partner becomes HIV positive
- have severe vaginal bleeding or bleeding that lasts a long time or concerns you

General advice about the safe and effective use of Skyla

Medicines are sometimes prescribed for conditions other than those listed in patient information leaflets. If you would like more information, talk with your healthcare provider. You can ask your healthcare provider for information about Skyla that is written for healthcare professionals.

What are the ingredients in Skyla?

Active ingredient: levonorgestrel

Inactive ingredients: silicone, polyethylene, silver, silica, barium sulfate, iron oxide

Manufactured for: Bayer HealthCare Pharmaceuticals Inc.

Whippany, NJ 07981

© 2013, Bayer HealthCare Pharmaceuticals Inc.

All rights reserved.

For more information, go to www.skyla-us.com or call 1-888-842-2937.

This Patient Information has been approved by the U.S. Food and Drug Administration. 7/2021

PACKAGE LABEL

Skyla (levonorgestrel-releasing intrauterine system) Carton

NDC 50419-422-01

1 Sterile Unit

IMPORTANT: To be inserted in the uterus by or under the supervision of a licensed clinician. See physician insert for detailed instructions for use.

Skyla

(levonorgestrel-releasing intrauterine system)

Rx only

— 13.5 mg levonorgestrel

— 1 sterile unit

— intrauterine use